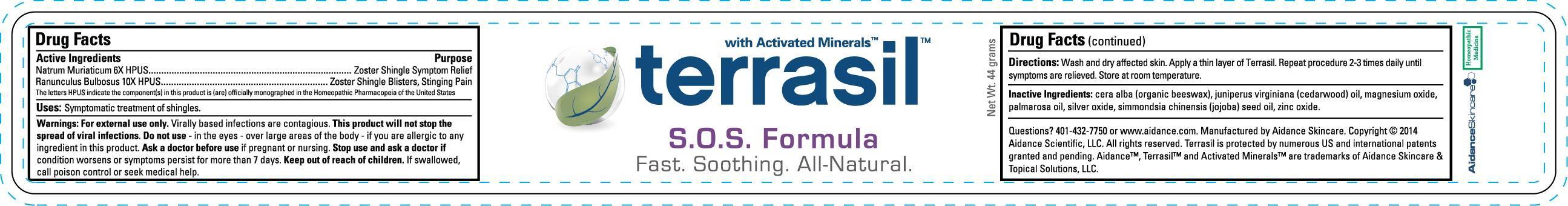 DRUG LABEL: Terrasil S.O.S. Formula
NDC: 24909-148 | Form: OINTMENT
Manufacturer: Aidance Skincare & Topical Solutions, LLC
Category: homeopathic | Type: HUMAN OTC DRUG LABEL
Date: 20140513

ACTIVE INGREDIENTS: RANUNCULUS BULBOSUS 10 [hp_X]/1 g; SODIUM CHLORIDE 6 [hp_X]/1 g
INACTIVE INGREDIENTS: JOJOBA OIL; JUNIPERUS VIRGINIANA OIL; MAGNESIUM OXIDE; PALMAROSA OIL; SILVER OXIDE; WHITE WAX; ZINC OXIDE

Drug Facts

Active Ingredients

Natrum Muriaticum 6X HPUS, Ranunculus Bulbosus 10X HPUS

The letters HPUS indicate the component(s) in this product is (are) officially monographed in the Homeopathic Pharmacopeia of the United States

Purpose

Natrum Muriaticum - Zoster Shingle Symptom Relief

Ranunculus Bulbosus - Zoster Shingle Blisters, Stinging Pain

Uses

Symptomatic treatment of shingles

Warnings

For external use only.
Virally based infections are contagious. This product will not stop the spread of viral infections.
Do not use - in the eyes - over large areas of the body - if you are allergic to any ingredient in this product.
Ask a doctor before use if pregnant or nursing.
Stop use and ask a doctor if condition worsens or symptoms persist for more than 7 days.

Keep out of reach of children.

If swallowed, call poison control or seek medical help.

Directions

Wash and dry affected skin. Apply a thin layer of Terrasil. Repeat procedure 2-3 times daily until symptoms are relieved. Store at room temperature.

Inactive Ingredients

cera alba (organic beeswax), juniperus virginiana (cedarwood) oil, magnesium oxide, palmarosa oil, silver oxide, simmondsia chinensis (jojoba) seed oil, zinc oxide

PRINCIPAL DISPLAY PANEL - 44g Label

terrasil with Activated Minerals

S.O.S. Formula
Fast. Soothing. All-Natural.